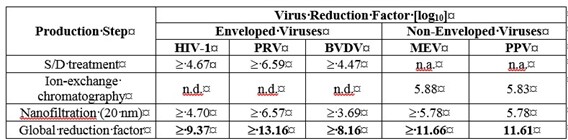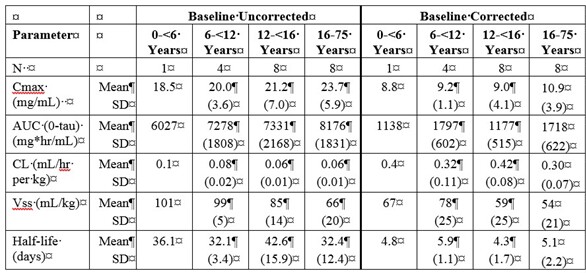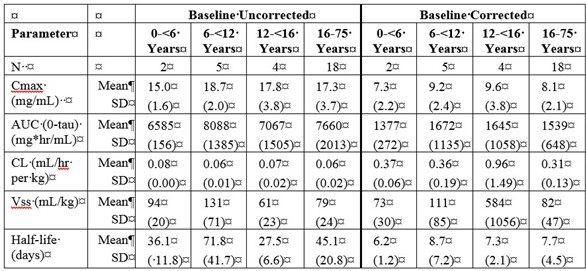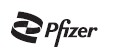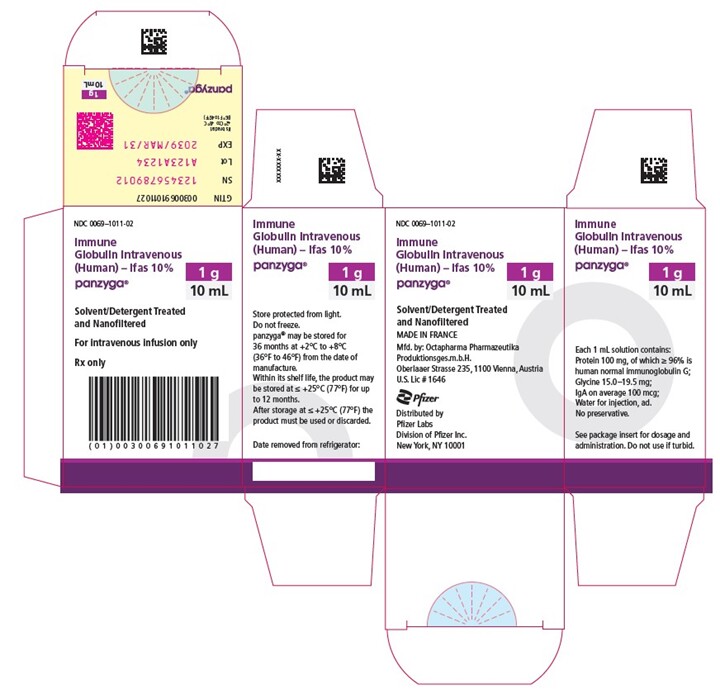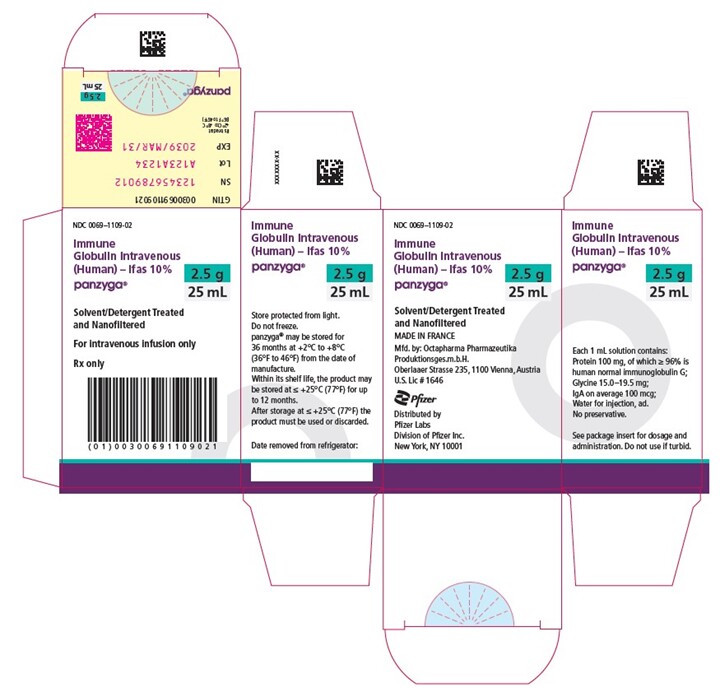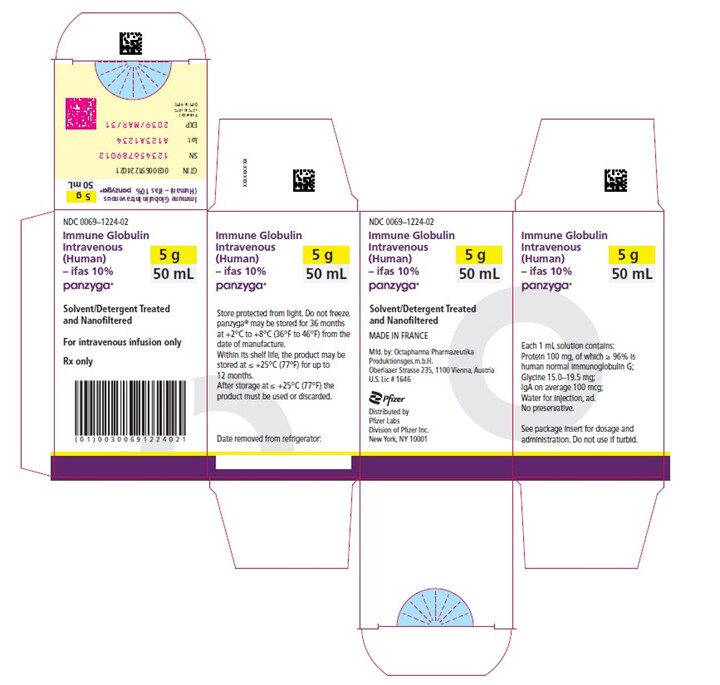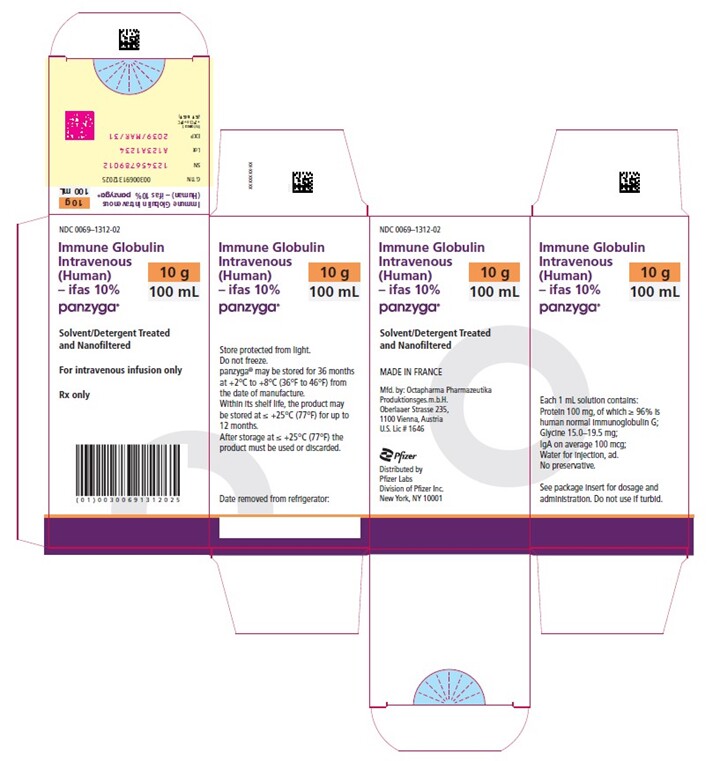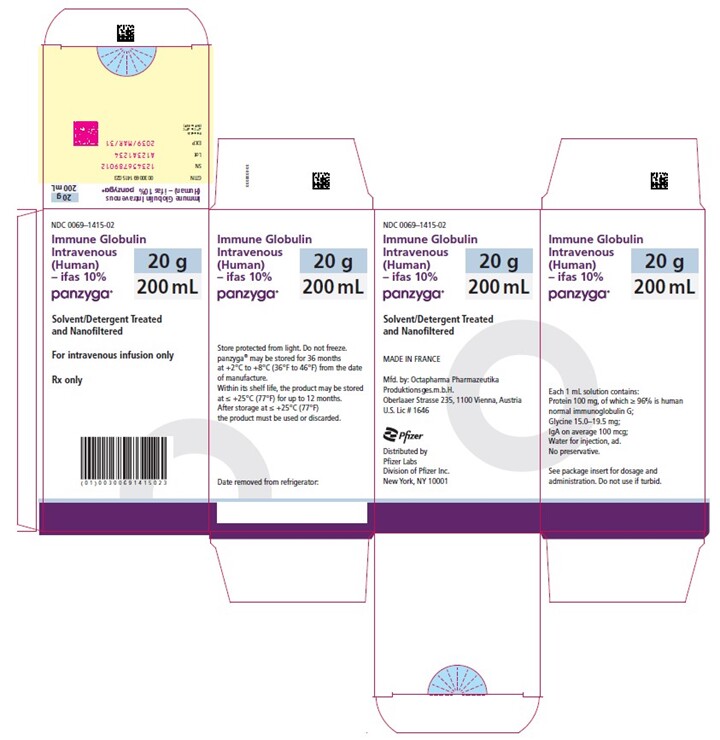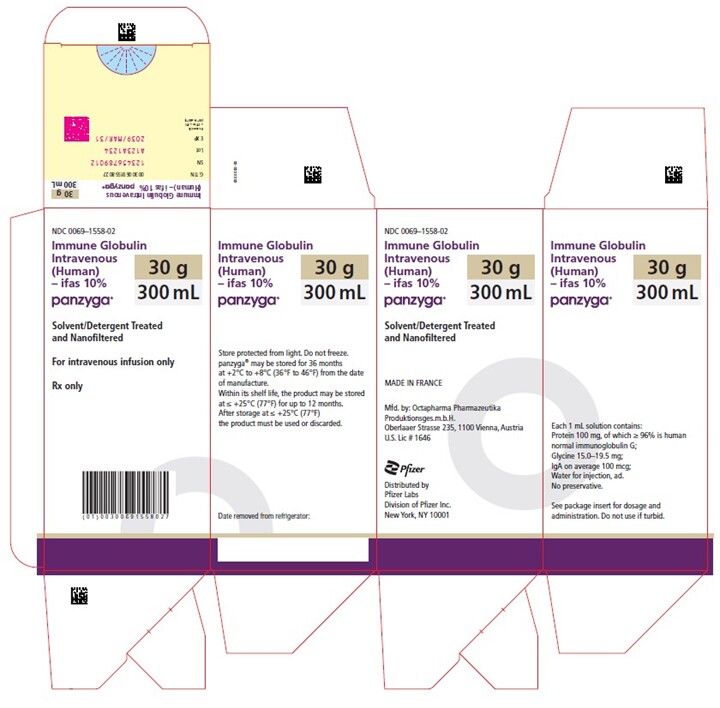 DRUG LABEL: Panzyga
NDC: 0069-1011 | Form: SOLUTION
Manufacturer: Pfizer Laboratories Div Pfizer Inc
Category: other | Type: PLASMA DERIVATIVE
Date: 20250508

ACTIVE INGREDIENTS: HUMAN IMMUNOGLOBULIN G 100 mg/1 mL

HIGHLIGHTS OF PRESCRIBING INFORMATION

These highlights do not include all the information needed to use PANZYGA safely and effectively. See full prescribing information for PANZYGA.
PANZYGA, (immune globulin intravenous, human - ifas)
10% Liquid Preparation
Initial U.S. Approval: 2018

RECENT MAJOR CHANGES

Indications and Usage (1) 01/2021

Dosage and Administration, Dose (2.1) 01/2021

WARNING: THROMBOSIS, RENAL DYSFUNCTION, and ACUTE RENAL FAILURE

See full prescribing information for complete boxed warning

- Thrombosis may occur with immune globulin intravenous (IGIV) products, including PANZYGA. Risk factors may include: advanced age, prolonged immobilization, hypercoagulable conditions, history of venous or arterial thrombosis, use of estrogens, indwelling vascular catheters, hyperviscosity, and cardiovascular risk factors.

- Renal dysfunction, acute renal failure, osmotic nephropathy, and death may occur with the administration of IGIV products in predisposed patients. Renal dysfunction and acute renal failure occur more commonly in patients receiving IGIV products containing sucrose. PANZYGA does not contain sucrose.

-For patients at risk of thrombosis, renal dysfunction, or renal failure, administer PANZYGA at the minimum infusion rate practicable. Ensure adequate hydration in patients before administration. Monitor for signs and symptoms of thrombosis and assess blood viscosity in patients at risk for hyperviscosity.

1 INDICATIONS AND USAGE

PANZYGA is an immune globulin intravenous (human) - ifas 10% liquid preparation indicated for the treatment of:

Primary humoral immunodeficiency (PI) in patients 2 years of age and older (1.1).

Chronic immune thrombocytopenia (ITP) in adults (1.2).

Chronic inflammatory demyelinating polyneuropathy (CIDP) in adults (1.3)

2 DOSAGE AND ADMINISTRATION

For intravenous use only (2).

Indication | Dose | Initial Infusion Rate | Maximum Infusion Rate (as tolerated)
PI | 300-600 mg/kg (3-6 mL/kg)every 3-4 weeks | 1 mg/kg/min (0.01 mL/kg/min) | 14 mg/kg/min (0.14 mL/kg/min)
Chronic ITP in adults | 2 g/kg (20 mL/kg), divided into 2 daily doses of 1 g/kg (10 mL/kg) given on 2 consecutive days | 1 mg/kg/min (0.01 mL/kg/min) | 8 mg/kg/min (0.08 mL/kg/min)
CIDP in adults | Loading dose: 2 g/kg (20 mL/kg), divided into 2 daily doses of 1 g/kg (10 mL/kg) given on 2 consecutive days Maintenance dose: 1-2 g/kg (10-20 mL/kg) every 3 weeks divided in 2 doses given over 2 consecutive days | 1 mg/kg/min (0.01 mL/kg/min) | 12 mg/kg/min (0.12 mL/kg/min)

Ensure that patients with pre-existing renal insufficiency are not volume depleted; discontinue PANZYGA if renal function deteriorates (2 , 5.2).

For patients at risk of renal dysfunction or thrombotic events, administer PANZYGA at the minimum dose and infusion rate practicable (5.2 , 5.4).

3 DOSAGE FORMS AND STRENGTHS

Solution containing 10% IgG (100 mg/mL) (3 , 16)

4 CONTRAINDICATIONS

History of anaphylactic or severe systemic reactions to human immune globulin (4)

IgAdeficient patients with antibodies against IgA and a history of hypersensitivity (4)

5 WARNINGS AND PRECAUTIONS

IgA-deficient patients with antibodies against IgA are at greater risk of developing severe hypersensitivity and anaphylactic reactions to PANZYGA. Epinephrine should be available immediately to treat any severe acute hypersensitivity reactions (5.1).

Monitor renal function, including blood urea nitrogen and serum creatinine, and urine output in patients at risk of developing acute renal failure (5.2).

Hyperproteinemia, increased serum osmolarity and hyponatremia may occur in patients receiving PANZYGA (5.3).

Hemolysis that is either intravascular or due to enhanced red blood cell sequestration can develop subsequent to PANZYGA treatments. Risk factors for hemolysis include high doses and non-O-blood group. Closely monitor patients for hemolysis and hemolytic anemia (5.6).

Aseptic Meningitis Syndrome may occur in patients receiving PANZYGA, especially with high doses or rapid infusion (5.5).

Monitor patients for pulmonary adverse reactions [transfusion-related acute lung injury (TRALI)] (5.7).

PANZYGA is made from human plasma and may contain infectious agents, e.g., viruses, variant Creutzfeldt-Jakob disease [vCJD] agent and, theoretically, the Creutzfeldt-Jakob disease agent (5.10).

6 ADVERSE REACTIONS

PI - The most common adverse reactions reported in greater than 5% of subjects during a clinical trial were: headache, nausea, fever, fatigue, and abdominal pain (6).

Chronic ITP in adults - The most common adverse reactions reported in greater than 5% of subjects during a clinical trial were: headache, fever, nausea, vomiting, dizziness, and anemia (6).

CIDP in adults – The most common adverse reactions reported in greater than 5% of subjects during a clinical trial were: headache, fever, dermatitis, blood pressure increased (6).

To report SUSPECTED ADVERSE REACTIONS, contact Pfizer Inc. at 1-800-438-1985 or FDA at 1-800-FDA-1088 or www.fda.gov/medwatch.

7 DRUG INTERACTIONS

The passive transfer of antibodies may confound the results of serological testing (7).

The passive transfer of antibodies may interfere with the immune response to live viral vaccines, such as measles, mumps, and rubella (7).

8 USE IN SPECIFIC POPULATIONS

Geriatric Use: In patients over age 65 years and in any patient at risk of developing renal insufficiency, infuse PANZYGA at the minimum infusion rate practicable and do not exceed the recommended dose PANZYGA (8.5).

_______________________________________________________________________________________________________________________________________

FULL PRESCRIBING INFORMATION

PANZYGA, Immune Globulin Intravenous (Human) - ifas

10% Liquid Preparation

WARNING: THROMBOSIS, RENAL DYSFUNCTION, and ACUTE RENAL FAILURE

Thrombosis may occur with immune globulin intravenous (IGIV) products, including PANZYGA. Risk factors may include: advanced age, prolonged immobilization, hypercoagulable conditions, history of venous or arterial thrombosis, use of estrogens, indwelling central vascular catheters, hyperviscosity, and cardiovascular risk factors. Thrombosis may occur in the absence of known risk factors. (See WARNING and PRECAUTIONS [ 5.4 ], PATIENT COUNSELING INFORMATION [ 17 ])

Renal dysfunction, acute renal failure, osmotic nephrosis, and death may occur in predisposed patients who receive IGIV products, including PANZYGA. Patients predisposed to renal dysfunction include those with a degree of pre-existing renal insufficiency, diabetes mellitus, age greater than 65, volume depletion, sepsis, paraproteinemia, or patients receiving known nephrotoxic drugs. Renal dysfunction and acute renal failure occur more commonly in patients receiving IGIV product containing sucrose. PANZYGA does not contain sucrose.

For patients at risk of thrombosis, renal dysfunction or acute renal failure, administer PANZYGA at the minimum dose and infusion rate practicable. Ensure adequate hydration in patients before administration. Monitor for signs and symptoms of thrombosis and assess blood viscosity in patients at risk for hyperviscosity. (See DOSAGE and ADMINISTRATION [ 2.3 ], WARNINGS and PRECAUTIONS [ 5.2 , 5.4 ])

1 INDICATIONS AND USAGE

1.1 Primary Humoral Immunodeficiency Diseases (PI)

PANZYGA is indicated for treatment of primary humoral immunodeficiency (PI) in patients 2 years of age and older. This includes, but is not limited to, congenital agammaglobulinemia, common variable immunodeficiency, X-linked agammaglobulinemia, Wiskott-Aldrich syndrome, and severe combined immunodeficiencies.

1.2 Chronic Immune Thrombocytopenia (ITP)

PANZYGA is indicated for the treatment of adult patients with ITP to raise platelet counts to control or prevent bleeding.

1.3 Chronic Inflammatory Demyelinating Polyneuropathy (CIDP)

PANZYGA is indicated for the treatment of adults with chronic inflammatory demyelinating polyneuropathy (CIDP) to improve neuromuscular disability and impairment.

2 DOSAGE AND ADMINISTRATION

For intravenous use only.

2.1 Dose

Indication | Dose | Initial Infusion Rate (first 30 min) | Maximum Infusion Rate (as tolerated)
Treatment of Primary Humoral Immunodeficiency (PI)* | 300 to 600 mg/kg body weight (3-6 mL/kg) administered every 3 to 4 weeks | 1 mg/kg/min (0.01 mL/kg/min) | 14 mg/kg/min (0.14 mL/kg/min)
Treatment of Chronic Immune Thrombocytopenia (ITP) | 2 g/kg (20 mL/kg), divided into 2 daily doses of 1 g/kg (10 mL/kg) given on 2 consecutive days | 1 mg/kg/min (0.01 mL/kg/min) | 8 mg/kg/min (0.08 mL/kg/min)
Treatment of Chronic Inflammatory Demyelinating Polyneuropathy (CIDP) | Loading Dose: 2 g/kg (20 mL/kg), divided into 2 daily doses of 1 g/kg (10 mL/kg) given on 2 consecutive days Maintenance dose: 1-2 g/kg (10-20 mL/kg) every 3 weeks divided in 2 daily doses given over 2 consecutive days | 1 mg/kg/min (0.01 mL/kg/min) | 12 mg/kg/min (0.12 mL/kg/min)

*Significant differences in the half-life of IgG among patients with PI may necessitate the dose and frequency of immunoglobulin therapy to vary from patient to patient. Determine the proper dose and frequency by monitoring the clinical response. Adjust dose over time to achieve the desired trough levels of IgG and clinical responses.

The initial infusion rate should be maintained for 30 min. Following the initial infusion, and if tolerated, the infusion rate may be gradually increased every 15-30 minutes, as tolerated to the maximum infusion rate shown in the table above for each indication.

Measles Exposure.

If a patient with primary humoral immunodeficiency has been exposed to measles, it may be prudent to administer an extra dose of IGIV as soon as possible and within 6 days of exposure. A dose of 400 mg/kg should provide a serum level > 240 mIU/mL of measles antibodies for at least two weeks.

If a patient with primary humoral immunodeficiency is at risk of future measles exposure and receives a dose of less than 530 mg/kg every 3-4 weeks, the dose should be increased to at least 530 mg/kg. This should provide a serum level of 240 mIU/mL of measles antibodies for at least 22 days after infusion.

2.2 Administration

- Inspect parenteral products visually for particulate matter and discoloration prior to administration, whenever solution and container permit. Do not use PANZYGA if it is turbid and/or if discoloration is observed. Using a needle, no larger than a 16-gauge needle, insert the needle only once within the stopper area (delineated by the raised ring for penetration). Penetrate the stopper perpendicularly to its plane and within the ring.
- PANZYGA bottles may be pooled under aseptic conditions into sterile infusion bags. Infuse within 8 hours after pooling.
- Administer at room or body temperature only by the intravenous route
- PANZYGA is not supplied with an infusion set. If a filtered infusion set is used (not mandatory), choose a filter size of 0.2-200 microns.
- Do not administer PANZYGA simultaneously with another intravenous preparation in the same infusion set, including immune globulin products from another manufacturer.
- After administration, the infusion line may be flushed with either normal saline or 5% dextrose in water.
- Monitor the patient carefully throughout the infusion. Certain adverse drug reactions are related to the rate of infusion, and will disappear promptly after slowing or stopping the infusion. In such cases, after symptoms subside, resume the infusion at a lower rate. Ensure that patients with pre-existing renal insufficiency are not volume depleted. For patients at risk of renal dysfunction or thromboembolic events, administer PANZYGA at the minimum infusion rate practicable [ see Warnings and Precautions (5.2, 5.4)] . Do not exceed 3.3 mg/kg/min (0.033 mL/kg/min). Discontinue if renal function deteriorates.

3 DOSAGE FORMS AND STRENGTHS

Solution containing 10% IgG (100 mg/mL) (See How Supplied/Storage and Handling (16)).

4 CONTRAINDICATIONS

- PANZYGA is contraindicated in patients who have a history of severe systemic hypersensitivity reactions, such as anaphylaxis, to human immunoglobulin.
- PANZYGA is contraindicated in IgA-deficient patients with antibodies against IgA and history of hypersensitivity .

5 WARNINGS AND PRECAUTIONS

5.1 Hypersensitivity

Severe hypersensitivity reactions may occur (See Contraindications (4)) . [ 1 ] In case of hypersensitivity, discontinue PANZYGA infusion immediately and institute appropriate treatment. Have epinephrine available for immediate treatment of severe acute hypersensitivity reactions.

PANZYGA contains trace amounts of IgA (average 100 µg/mL in a 10% solution). IgA-deficient patients with antibodies against IgA are at greater risk of developing severe hypersensitivity and anaphylactoid reactions when administered PANZYGA (See Contraindications (4)) .

5.2 Renal Failure

Renal dysfunction, acute renal failure, osmotic nephropathy, and death may occur upon use of PANZYGA in predisposed patients.

Ensure that patients are not volume depleted prior to the initiation of the infusion of PANZYGA.

For patients at risk of renal dysfunction because of pre-existing renal insufficiency or predisposition to acute renal failure (such as individuals with diabetes mellitus, age greater than 65 years, volume depletion, sepsis, paraproteinemia, or those receiving known nephrotoxic drugs), administer PANZYGA at the minimum infusion rate practicable (See Boxed Warning, and Dosage and Administration (2)).

Periodic monitoring of renal function tests and urine output is particularly important in patients judged to be at risk of developing acute renal failure. Assess renal function, including a measurement of blood urea nitrogen (BUN)/serum creatinine, prior to the initial infusion of PANZYGA and again at appropriate intervals thereafter. If renal function deteriorates, consider discontinuation of the product.

5.3 Hyperproteinemia, Increased Serum Viscosity and Hyponatremia

Hyperproteinemia, increased serum viscosity and hyponatremia may occur in patients receiving PANZYGA therapy. It is clinically critical to distinguish true hyponatremia from pseudohyponatremia related to hyperproteinemia with concomitant decreased calculated serum osmolality or elevated osmolar gap, because treatment aimed at decreasing serum free water in patients with pseudohyponatremia may lead to volume depletion, a further increase in serum viscosity and a higher risk of thromboembolic events.[ 2 ]

5.4 Thrombotic Events

Thrombosis may occur following treatment with immune globulin products, including PANZYGA. Risk factors include: advanced age, prolonged immobilization, hypercoagulable conditions, history of venous or arterial thrombosis, use of estrogens, indwelling central vascular catheters, hyperviscosity, and cardiovascular risk factors. Thrombosis may occur in the absence of known risk factors.

Consider baseline assessment of blood viscosity in patients at risk for hyperviscosity, including those with cryoglobulins, fasting chylomicronemia / markedly high triacylglycerols (triglycerides), or monoclonal gammopathies. For patients at risk of thrombotic events, administer PANZYGA at the minimum dose and infusion rate practicable. Ensure adequate hydration in patients before administration. Monitor for signs and symptoms of thrombosis and assess blood viscosity in patients at risk for hyperviscosity.[ 3-5 ] (See BOXED WARNING, DOSAGE and ADMINSTRATION [ 2 ], PATIENT COUNSELING INFORMATION [ 17 ])

5.5 Aseptic Meningitis Syndrome

Aseptic meningitis syndrome (AMS) may occur with PANZYGA treatment. Discontinuation of treatment has resulted in remission of AMS within several days without sequelae. The syndrome usually begins within several hours to two days following infusion with PANZYGA. It is characterized by symptoms and signs including severe headache, nuchal rigidity, drowsiness, fever, photophobia, painful eye movements, nausea, and vomiting. Cerebrospinal fluid (CSF) studies frequently reveal pleocytosis up to several thousand cells per cubic millimeter, predominantly from the granulocytic series, and elevated protein levels up to several hundred mg/dl, but negative culture results. Conduct a thorough neurological examination in patients exhibiting such symptoms and signs, including CSF studies, to rule out other causes of meningitis. Patients with a history of migraine may be more susceptible.[ 6 ]

AMS may occur more frequently following high doses (≥ 2 g/kg) and/or rapid infusion of IGIV.

5.6 Hemolysis

PANZYGA may contain blood group antibodies that can act as hemolysins and induce in vivo coating of red blood cells (RBCs) with immunoglobulin, causing a positive direct antiglobulin test (DAT) (Coombs’ test) result and hemolysis. Delayed hemolytic anemia can develop subsequent to IGIV therapy due to enhanced RBC sequestration and acute hemolysis, consistent with intravascular hemolysis, has been reported. Cases of severe hemolysis-related renal dysfunction/failure or disseminated intravascular coagulation have occurred following infusion of IGIV.

The following risk factors may be associated with the development of hemolysis following IGIV administration: high doses (e.g., 2 g/kg or more), given either as a single administration or divided over several days, and non-O blood group.[ 7 ] Other individual patient factors, such as an underlying inflammatory state (as may be reflected by, for example, elevated C-reactive protein or erythrocyte sedimentation rate), have been hypothesized to increase the risk of hemolysis following administration of IGIV [ 8 ], but their role is uncertain. Hemolysis has been reported following administration of IGIV for a variety of indications, including ITP.

Closely monitor patients for clinical signs and symptoms of hemolysis, particularly patients with risk factors noted above. Consider appropriate laboratory testing in higher risk patients, including measurement of hemoglobin or hematocrit prior to infusion and within approximately 36 to 96 hours post-infusion. If clinical signs and symptoms of hemolysis or a significant drop in hemoglobin or hematocrit have been observed, perform confirmatory laboratory testing, including direct antiglobulin test. If transfusion is indicated for patients who develop hemolysis with clinically compromising anemia after receiving IGIV, perform adequate cross-matching to avoid exacerbating on-going hemolysis.

5.7 Transfusion-Related Acute Lung Injury (TRALI)

Noncardiogenic pulmonary edema [Transfusion-Related Acute Lung Injury (TRALI)] may occur in patients administered IGIV.[ 9 ] TRALI is characterized by severe respiratory distress, pulmonary edema, hypoxemia, normal left ventricular function, and fever. Signs and symptoms typically appear within 1 to 6 hours after transfusion. Patients with TRALI may be managed using oxygen therapy with adequate ventilatory support.

Monitor recipients for pulmonary adverse reactions. If TRALI is suspected, perform appropriate tests for the presence of anti-HLA and anti-neutrophil antibodies in both the product and patient’s serum.

5.8 Hypertension

Elevations of systolic blood pressure to 180 mm Hg or more and/or of diastolic blood pressure to more than 120 mm Hg (hypertensive urgency) can be observed during and/or shortly following infusion of IGIV. Such elevations are reported more often among patients with a history of hypertension. Check patients for a history of hypertension and current antihypertensive medication use. Monitor blood pressure prior to, during, and following PANZYGA infusion.

5.9 Volume Overload

Carefully consider the relative risks and benefits before prescribing the high dose regimen (for chronic ITP) in patients at increased risk of volume overload.

5.10 Transmission of Infectious Agents

Because PANZYGA is made from human blood, it may carry a risk of transmitting infectious agents, e.g., viruses and theoretically, the variant Creutzfeldt-Jakob disease and Creutzfeldt-Jakob disease (CJD) agent. The risk of infectious agent transmission has been reduced by screening plasma donors and by including virus inactivation/removal steps in the manufacturing process of PANZYGA. Report all infections thought by a physician or other healthcare provider to have been possibly transmitted by this product to Pfizer Inc. at 1-800-438-1985. Discuss the risks and benefits of PANZYGA with the patient before prescribing or administering this product.

5.11 Monitoring Laboratory Tests

- After infusion of immunoglobulin, the transitory rise of the passively transferred antibodies in the patient’s blood may yield positive serological testing results, with the potential for misleading interpretation.
- Passive transmission of antibodies to erythrocyte antigens (e.g., A, B, and D) may cause a positive direct or indirect antiglobulin (Coombs’) test. Clinically assess patients with known renal dysfunction, diabetes mellitus, age greater than 65 years, volume depletion, sepsis, paraproteinemia, or those receiving nephrotic agents, and monitor as appropriate (BUN; serum creatinine, urine output) during therapy with PANZYGA.
- Consider baseline assessment of blood viscosity in patients at risk for hyperviscosity, including those with polycythemia, cryoglobulins, fasting chylomicronemia/markedly high triglycerides, or monoclonal gammopathies.
- Consider measuring hemoglobin or hematocrit at baseline and approximately 36 to 96 hours post-infusion in patients at higher risk of hemolysis. If signs and/or symptoms of hemolysis are present after an infusion of PANZYGA, perform appropriate laboratory testing for confirmation.
- If TRALI is suspected, perform appropriate tests for the presence of anti-neutrophil antibodies in both the product and patient’s serum.

6 ADVERSE REACTIONS

PI: The most common adverse reactions observed at a rate of more than 5% in subjects in clinical trials were: headache, abdominal pain, fever, nausea, and fatigue.

Chronic ITP in adults: The most common adverse reactions observed at a rate of more than 5% in subjects in clinical trials were: headache, fever, nausea, vomiting, dizziness, and anemia.

CIDP in adults: The most common adverse reactions observed at a rate of more than 5% in subjects in clinical trials were: headache, fever, dermatitis and blood pressure increased.

The most serious adverse reaction observed with PANZYGA treatment during clinical trials was aseptic meningitis in one subject.

6.1 Clinical Trials Experience

Because clinical trials are conducted under widely varying conditions, adverse reaction rates observed in the clinical trials of a product cannot be directly compared to rates in the clinical trials of another product and may not reflect the rates observed in clinical practice.

Treatment of Primary Humoral Immunodeficiency (PI)

In a prospective, open-label, single-arm, multicenter study in 51 children and adults with PI, subjects received PANZYGA at a dose between 200 to 800 mg/kg body weight every 3 or 4 weeks. Subjects participated in the study for a mean of 360 days. Infusions were initiated at a rate of 1 mg/kg/minute for the first 30 minutes, and, if tolerated, could be advanced to a maximum tolerated rate not exceeding 8 mg/kg/minute. The mean age of subjects was 26.8 years (range: 2 to 65 years).

This study was followed by an extension study that evaluated the safety of PANZYGA administered at higher infusion rates in 21 subjects that successfully had completed the first study. Nineteen of the 21 enrolled patients received PANZYGA up to the maximum allowed infusion rate of 14 mg/kg/minute. In the extension study, medication-related adverse events were reported in 4 of 21 subjects (19%). Adverse reactions occurring in more than 5% of subjects were nausea (9.5%) and headache (9.5%).

In the study in PI, infusion-related adverse events (during or within 72 hours after the end of infusion) were reported in 16 patients (76%) enrolled in the 3-weeks treatment schedule and in 22 patients (73%) in the 4-weeks treatment schedule. Overall, 38 infusions (5%) had at least one adverse event considered related to study medication: 5 infusions (3%) in children, 4 infusions in adolescents (2%), and 29 infusions (8%) in adults. Study medication-related (possible or probable) infusion-related adverse reactions were associated with 35 infusions (5%) (overall); study medication-related headache was noted in 21 infusions (3%).

Table 1: Adverse Reactions* Occurring in more than 5% of Subjects with PI

Adverse Reaction | No. of Subjects with Adverse Reaction(percentage of subjects)
Headache | 11 (22%)
Abdominal pain (upper) | 7 (14%)
Fever | 7 (14%)
Nausea | 5 (10%)
Sinusitis | 4 (8%)
Fatigue | 3 (6%)
Bronchitis | 3 (6%)

* Any infusional and any study medication related adverse events.

Treatment of Chronic Immune Thrombocytopenia (ITP) in Adults

In a prospective, open-label, single-arm, multicenter study, 40 adult subjects with chronic ITP received PANZYGA at a dose of 2 g/kg, administered daily as 1 g/kg intravenous infusions on 2 consecutive days. 3/40 subjects did not receive a second infusion of PANZYGA due to infusion reactions, including chills, headache, fever and nausea. All subjects except 1 received at least 1 infusion with the highest rate of 8 mg/kg/minute. Pre-medication to alleviate potential adverse drug reactions was not allowed in the study.

There were 67 treatment emergent adverse events (TEAEs) reported in 24 (60%) subjects that were related to administration of PANZYGA. 55 of these adverse events (82%) were infusional adverse events that occurred within 72 hours after start of the infusion. Seven of these adverse events in 2 subjects were severe. These included headache, nausea, vomiting and chills.

When analyzed by infusion, infusion-related adverse events were reported in 33 of the 77 infusions (43%).

Table 2: Adverse Reactions* Occurring in more than 5% of Subjects with Chronic ITP in Adults

Adverse Reaction | No. of Subjects with Adverse Reaction(percentage of subjects)
Headache | 20 (50%)
Fever | 9 (23%)
Nausea | 7 (18%)
Vomiting | 4 (10%)
Dizziness | 4 (10%)
Anemia | 4(10%)

* Any infusional and any study medication related adverse events.

One out of 40 subjects with ITP treated with PANZYGA developed aseptic meningitis on Day 2 of the infusion. This subject was managed with antibiotics and supportive care with recovery.

Baseline direct Coomb’s test was performed in 39/40 subjects that were treated with PANZYGA. 10/39 (26%) subjects subsequently developed positive Coomb’s test. One subject was not tested at baseline but had positive results on all 3 subsequent visits. Four of these subjects (10%) developed hemolytic anemia after receiving PANZYGA. These resolved spontaneously without any intervention.

Treatment of Chronic Inflammatory Demyelinating Polyneuropathy in Adults

In a prospective, double-blind, randomized, multicenter study, 142 adult subjects with CIDP aged between 18 and 83 years were enrolled and randomized 1:2:1 to receive first a loading dose of 2 g/kg and then 0.5 g/kg, 1.0 g/kg or 2.0 g/kg PANZYGA for 7 maintenance infusions at 3-week intervals during the 24-week Dose-evaluation Phase (mean doses administered - including loading and rescue doses - were 0.91, 1.24 and 1.97 g/kg for 0.5, 1 and 2g/kg group, respectively).

All 142 subjects in this study received at least 1 dose of PANZYGA. The median maximum infusion rate was 0.12 mL/kg/min throughout the study in all dose groups. Seventy-three out of the 142 subjects experienced a total of 209 adverse reactions (AR). Table 3 summarizes the most frequent ARs that occurred in more than 5% of subjects. Generally, the incidence of ARs was similar across the dose groups; the only AR where a dose effect was evident was headache, with an incidence of 2.9% in the 0.5 g/kg group, 14.5% in the 1.0 g/kg group and 23.7% in the 2.0 g/kg group. Pre-medication for AEs was only allowed in subjects who had adverse events during 2 consecutive infusions. During the study 11 subjects (7.75%) received premedication.

Table 3: Adverse Reactions* Occurring in more than 5% of Adult Subjects with CIDP

Adverse Reaction | No. of Subjects with Adverse Reaction(percentage of subjects)
Headache | 21 (14.8 %)
Fever | 20 (14.1%)
Dermatitis | 14 (9.9%)
Blood Pressure Increased | 11 (7.7%)

* Any infusional and any study medication related adverse events.

Two serious adverse reactions (headache and vomiting) were reported in one subject but did not lead to discontinuation of PANZYGA.

6.2 Postmarketing Experience

The following adverse reactions have been identified during post-approval use of PANZYGA. Because these adverse reactions are reported voluntarily from a population of uncertain size, it is not always possible to reliably estimate their frequency or establish a causal relationship to drug exposure:

Blood and lymphatic system disorders
Leucopenia, hemolysis, pancytopenia

Immune system disorders
Hypersensitivity (e.g., anaphylaxis), anaphylactic shock, anaphylactic reaction, anaphylactoid reaction, allergic reaction, angioedema, face edema

Metabolic and nutritional disorders
Fluid overload, (pseudo)hyponatremia

Psychiatric disorders
Agitation, confusional state, anxiety, nervousness

Nervous system disorders
Coma, loss of consciousness, seizures, (acute) encephalopathy, cerebrovascular accident, stroke, aseptic meningitis, migraine, speech disorder, paraesthesia, hypoesthesia, photophobia, tremor

Cardiac disorders
Myocardial infarction, cardiac arrest, angina pectoris, tachycardia, bradycardia, palpitations, cyanosis

Vascular disorders
Hypotension, (deep vein) thrombosis, peripheral circulatory failure/collapse, hypertension, phlebitis, pallor

Respiratory, thoracic and mediastinal disorders
Apnea, Acute Respiratory Distress Syndrome (ARDS), TRALI, respiratory failure, pulmonary embolism, pulmonary edema, bronchospasm, dyspnea, hypoxia, wheezing, cough

Gastrointestinal disorders
Diarrhea, hepatic dysfunction, abdominal discomfort

Skin and subcutaneous tissue disorders
Eczema, urticaria, rash (erythematous), pruritus, alopecia, Stevens-Johnson syndrome, epidermolysis, skin exfoliation, erythema (multiforme), dermatitis (e.g., bullous dermatitis)

Musculoskeletal and connective tissue disorders
Back pain, arthralgia, myalgia, musculoskeletal pain, muscle stiffness, pain in extremity, neck pain, muscle spasm

Renal and urinary disorders
Acute renal failure, osmotic nephropathy, renal pain

General disorders and administration site conditions
Injection site reaction, chills, chest pain or discomfort, hot flush, flushing, flu-like illness, feeling cold or hot, edema, hyperhidrosis, malaise, asthenia, lethargy, burning sensation

Investigations
Hepatic enzymes increased, oxygen saturation decreased, falsely elevated erythrocyte sedimentation rate, positive direct antiglobulin (Coombs’) test

7 DRUG INTERACTIONS

Clinical studies have not evaluated mixtures of PANZYGA with other drugs and intravenous solutions. It is recommended that PANZYGA is administered separately from other drugs or medications which the patient may be receiving. Do not mix the product.

Do not mix PANZYGA with IGIVs from other manufacturers.

Passively transferred antibodies in immunoglobulin preparations can confound the results of serological testing, e.g. false positive Treponema pallidum testing might occur.

Antibodies in PANZYGA may interfere with the response to live viral vaccines, such as measles, mumps, and rubella. Inform physicians of recent therapy with PANZYGA, so that administration of live viral vaccines, if indicated, can be appropriately delayed for 3 or more months from the time of PANZYGA administration.

8 USE IN SPECIFIC POPULATIONS

8.1 Pregnancy

Risk Summary

No human data are available to indicate the presence or absence of drug-associated risk. Animal reproduction studies have not been conducted with PANZYGA. It is also not known whether PANZYGA can cause fetal harm when administered to a pregnant woman or can affect reproduction capacity. Immune globulins cross the placenta from maternal circulation increasingly after 30 weeks of gestation. In the U.S. general population, the estimated background risk of major birth defects and miscarriage in clinically recognized pregnancies is 2-4% and 15-20%, respectively.

8.2 Lactation

Risk summary

No human data are available to indicate the presence or absence of drug-associated risk. The developmental and health benefits of breastfeeding should be considered along with the mother’s clinical need for PANZYGA and any potential adverse effects on the breastfed infant from PANZYGA or from the underlying maternal condition.

8.4 Pediatric Use

Treatment of Primary Humoral Immunodeficiency (PI)

PANZYGA was evaluated in 25 pediatric subjects (age range: 2-15 years). Twenty-five percent of PI subjects exposed to PANZYGA were children (between 2 and 12 years of age). Pharmacokinetics, efficacy and safety were similar to those in adults. No specific dose requirements were necessary to achieve the targeted serum IgG levels in the pediatric subjects.

Treatment of Immune Thrombocytopenia (ITP) in children

The safety and effectiveness of PANZYGA have not been established in pediatric patients with ITP.

Treatment of Chronic Inflammatory Demyelinating Polyneuropathy (CIDP) in children

The safety and effectiveness of PANZYGA have not been established in pediatric patients with CIDP.

8.5 Geriatric Use

Clinical studies of PANZYGA in PID and ITP did not include sufficient numbers of subjects older than 65 years to determine whether they respond differently from younger subjects.

In the clinical study the safety and effectiveness of PANZYGA in subjects with CIDP older than 65 years was similar to those 65 years of age and younger. A total of 36 subjects older than 65 years were included in the clinical trial.

Patients older than 65 years of age may be at increased risk for developing adverse reactions such as thromboembolic events and acute renal failure (See Boxed Warnings and Thrombotic Events (5.4) and Renal Failure (5.2) . Do not exceed recommended doses in this population, and apply the minimum practicable infusion rate.

10 OVERDOSAGE

With intravenous administration, overdose may lead to fluid overload and hyperviscosity. Patients at risk of complications of fluid overload and hyperviscosity include elderly patients and those with cardiac or renal impairment.

11 DESCRIPTION

Immune Globulin Intravenous (Human), PANZYGA, is a solvent/detergent (S/D)-treated, sterile preparation of highly purified immunoglobulin G (IgG) derived from large pools of human plasma. PANZYGA is a solution for infusion to be administered intravenously.

This preparation contains approximately 100 mg of protein per mL (10%), of which not less than 96% is normal human immunoglobulin G. PANZYGA contains not more than 3% aggregates, not less than 94% monomers and dimers, and not more than 4% fragments. On average, the product contains 100 µg/mL of IgA, and lower amounts of IgM.

PANZYGA contains only trace amounts of sodium, and the pH is between 4.5 and 5.0. The osmolality is in the range of 240-310 mosmol/kg.

The manufacturing process for PANZYGA isolates IgG without additional chemical or enzymatic modification, and the Fc portion is maintained intact. PANZYGA contains the IgG antibody activities present in the donor population. IgG subclasses are fully represented with the following approximate percents of total IgG: IgG 1 is 65%, IgG 2 is 28%, IgG 3 is 3% and IgG 4 is 4%.

PANZYGA contains a broad spectrum of IgG antibodies against bacterial and viral agents that are capable of opsonization and neutralization of microbes and toxins. PANZYGA contains glycine (15.0-19.5 mg/mL), but no preservatives or sucrose.

All units of human plasma used in the manufacture of PANZYGA are provided by FDA-approved blood and plasma establishments, and are tested by FDA-licensed serological tests for HBsAg, antibodies to HCV and HIV and Nucleic Acid Test (NAT) for HCV and HIV1 and found to be non-reactive (negative).

The product is manufactured by the cold ethanol fractionation process followed by purification methodologies, as well as S/D treatment and nanofiltration (20 nm). The S/D mixture used is composed of tri-n-butyl phosphate (TNBP, solvent) and Triton X-100 (Octoxynol, detergent). The PANZYGA manufacturing process shows significant viral reduction and inactivation, demonstrated by in vitro infectivity studies (Table 4). The virus safety of PANZYGA is achieved through a combination of various process steps, including S/D treatment, ion-exchange chromatography, and nanofiltration (20 nm).

Table 4 shows the virus clearance during the manufacturing process for PANZYGA, expressed as the mean log 10 reduction factor (LRF).

Table 4: Virus Reduction by PANZYGA Manufacturing Process

HIV-1: Human Immunodeficiency Virus – 1, a model for HIV-1 and HIV-2;

PRV: Pseudorabies Virus, a model for large enveloped DNA viruses (e.g., herpes virus);

BVDV: Bovine Viral Diarrhea Virus, a model for e.g., Hepatitis C virus (HCV) and West-Nile virus (WNV);

MEV: Mouse Encephalomyelitis virus, a model for Hepatitis A virus (HAV);

PPV: Porcine Parvovirus, a model for Human Parvovirus B19;

n.a.: not applicable;

n.d: not done.

Additionally, the manufacturing process was investigated for its capacity to decrease the infectivity of an experimental agent of transmissible spongiform encephalopathy (TSE), considered as a model for the vCJD and CJD agents. [ 10 ]

Several of the individual production steps in the PANZYGA manufacturing process were shown to decrease TSE infectivity of that experimental model agent. TSE reduction steps include ion-exchange chromatography and nanofiltration, which together give a total of at least 10.4 log10 decrease of infectivity. These studies provide reasonable assurance that low levels of CJD/vCJD agent infectivity, if present in the starting material, would be removed.

12 CLINICAL PHARMACOLOGY

12.1 Mechanism of Action

Treatment of Primary Humoral Immunodeficiency (PI)

PANZYGA supplies a broad spectrum of opsonic and neutralizing IgG antibodies against bacteria or their toxins. The mechanism of action in PI has not been fully elucidated.

Treatment of Chronic Immune Thrombocytopenia (ITP) in Adults

The mechanism of action of immunoglobulins in the treatment of chronic ITP in adults has not been fully elucidated.

Treatment of Chronic Inflammatory Demyelinating Polyneuropathy (CIDP) in Adults

The mechanism of action of immunoglobulins in the treatment of CIDP in adults has not been fully elucidated.

12.2 Pharmacodynamics

PANZYGA contains mainly immunoglobulin G (IgG) with a broad spectrum of antibodies against various infectious agents reflecting the IgG activity found in the donor population. PANZYGA which is prepared from pooled material from not less than 1000 donors, has an IgG subclass distribution similar to that of native human plasma. Adequate doses of IGIV can restore abnormally low IgG level to the normal range. Standard pharmacodynamic studies were not performed.

12.3 Pharmacokinetics

Treatment of Primary Humoral Immunodeficiency (PI)

In the PI study, 50 pediatric and adult subjects underwent pharmacokinetic assessments. Subjects received infusions of PANZYGA (200 to 800 mg/kg body weight) every 3 or 4 weeks for 12 months. Blood samples for PK study were collected between the 7 th and 9 th PANZYGA infusion, depending on the individual treatment schedule.

Table 5a and 5b summarize the pharmacokinetic parameters of PANZYGA, based on serum concentrations of total IgG, in subjects receiving infusions every 3, or 4 weeks, respectively.

Table 5: PI Study- Pharmacokinetic Parameters of PANZYGA in Subjects

a) PK Parameters: IgG Arm: 3-weeks

b) PK Parameters: IgG Arm: 4-weeks

Treatment of Chronic Immune Thrombocytopenia (ITP) in Adults

Pharmacokinetic studies with PANZYGA have not been performed in adults with chronic ITP.

Treatment of Chronic Inflammatory Demyelinating Polyneuropathy (CIDP) in Adults

Pharmacokinetic studies with PANZYGA have not been performed in adult patients with CIDP.

The IgG trough levels were evaluated at each visit (Table 6) before the PANZYGA infusion. There was the option of rescue treatment with two consecutive infusions of 2.0 g/kg Panzyga at 3-week intervals (±4 days) for all subjects in the 0.5 and 1.0 g/kg Panzyga arms who were either stable at Week 6 or deteriorated after Week 3 and before Week 18. The actual administered dose for the three dose arms was: 0.91 ± 0.4 (n=35), 1.24 ± 0.2 (n=69) and 1.97 ± 0.2 (n=38) g/kg for 0.5, 1 and 2g/kg, respectively. There were no major differences among the three dose arms in demographic characteristics and baseline IgG levels. The percentage of increase in mean IgG from baseline to the end of study assessment was 46% in the 0.5 g/kg arm, 57% in the 1.0 g/kg arm and 91% in the 2.0 g/kg arm (Table 6).

Table 6 Mean IgG trough levels in subjects with CIDP

IgG troughs (g/L) |  | PANZYGA 0.5 g/kg | PANYZGA 1.0 g/kg | PANZYGA 2.0 g/kg
Visit / Time point |  | (N=35) | (N=69) | (N=38)
Visit 2 - Week 0 | Mean (SD) | 10.6 (3.1) | 10.5 (2.5) | 10.2 (3.0)
Visit 3 - Week 3 | Mean (SD) | 17.9 (3.5) | 17.1 (3.1) | 16.5 (3.3)
Visit 4 - Week 6 | Mean (SD) | 15.5 (3.0) | 16.5 (3.3) | 18.5 (4.0)
Visit 5 - Week 9 | Mean (SD) | 15.6 (3.3) | 16.5 (3.0) | 19.2 (4.4)
Visit 6 - Week 12 | Mean (SD) | 14.2 (2.6) | 16.8 (3.8) | 19.6 (4.3)
Visit 7 - Week 15 | Mean (SD) | 14.1 (2.7) | 16.2 (3.4) | 19.7 (4.4)
Visit 8 - Week 18 | Mean (SD) | 14.1 (2.3) | 15.9 (3.1) | 19.6 (5.2)
Visit 9 - Week 21 | Mean (SD) | 14.3 (2.3) | 16.0 (3.0) | 18.9 (3.5)
End of Study - Week 24 | Mean (SD) | 15.5 (3.6) | 16.5 (3.3) | 19.5 (4.6)

13 NONCLINICAL TOXICOLOGY

13.1 Carcinogenesis, Mutagenesis, Impairment of Fertility

No animal studies were conducted on carcinogenesis, mutagenesis, or impairment of fertility with PANZYGA.

13.2 Animal Toxicology and/or Pharmacology

Several standard nonclinical proof-of-concept and safety studies were performed with PANZYGA in animals. These included acute toxicity, pharmacokinetic, local tolerance, and safety pharmacology studies. PANZYGA. There were no adverse effects attributed to PANZYGA in the animal studies.

TNBP and Octoxynol-9 may be found in PANZYGA in trace amounts. In single- and repeated-dose toxicity studies in animals, these impurities caused no adverse effects when administered (alone or in combination) at doses multiple times higher than the equivalent human dose. A mixture of these compounds did not show teratogenic effects when administered to pregnant rabbits and rats during organogenesis.

14 CLINICAL STUDIES

14.1 Treatment of Primary Humoral Immunodeficiency (PI)

Study 1: In a prospective, open-label, single-arm, multicenter study in 51 children and adults with PI, subjects received PANZYGA at a dose between 200 to 800 mg/kg body weight every 3 or 4 weeks. Subjects participated in the study for a mean of 360 days. Infusions were initiated at a rate of 1 mg/kg/min for the first 30 minutes, and, if tolerated, could be advanced to a maximum tolerated rate not exceeding 8 mg/kg/min. The mean age of subjects was 26.8 years (range: 2 to 65 years).

The primary efficacy endpoint was the number of episodes of serious bacterial infections per patient per year. Serious infection included pneumonia, bacteremia or sepsis, osteomyelitis/septic arthritis, visceral abscesses, or bacterial meningitis. Secondary efficacy variables included: occurrence of any infection of any kind or seriousness; time to resolution of infections; use of antibiotics; the number of days of work/school missed; the number and days of hospitalizations; and the number of episodes of fever.

For the primary endpoint, the observed rate was 0.08 serious bacterial infections per patient per year (4 infections over 50.2 patient-years).

Only 1 adult patient was hospitalized due to an infection for 4 days (overall rate of days in hospital per person-year: 0.080). Episodes of fever were observed for less than 25% of all patients. The mean resolution time was 14 days for serious bacterial infections and 18 days for other infections. Approximately 50% of all patients missed at least 1 day of work or school due to infections, with an annual rate of less than 4 days/person-year.

Table 7 summarizes the efficacy results for all 51 subjects.

Table 7: Study 1 – Summary of Efficacy Results for subjects with PI

Category | Result | Unit
Number of subjects | 51 | Subjects
Total number of subject days | 18,349 | Days
Annual rate of confirmed serious bacterial infections (SBIs)* | 0.080 | SBIs/person-year **
Annual rate of other infections | 3.682 | Inf./person-year
Number of subjects (%) with use of antibiotics | 42 (82.4%) | Subjects(%)
Annual rate of use of antibiotics | 87 | Days/person-year
Absences from work or school due to Infection, number of days (%) | 183 (1.0%) | Days (%)
Annual rate of absences from work or school due to infection | 3.6 | Days/person-year
Hospitalization due to infection, number of days | 4 | Days
Annual rate of hospitalizations due to infection | 0.1 | Day/person-year

* Defined as bacteremia/sepsis, bacterial meningitis, osteomyelitis/septic arthritis, bacterial pneumonia and visceral abscess

** Upper 1-sided 99% confidence interval: 0.503

Throughout the entire study, the serum IgG trough levels were nearly constant for both treatment schedules and were above the required trough levels of about 5-6 g/L. The calculated pharmacokinetic parameters showed that the minimum concentration of IgG was at least 6.8 g/L for both treatment intervals.

14.2 Treatment of Chronic Immune Thrombocytopenia (ITP) in Adults

A prospective, open-label, single-arm, multicenter study assessed the efficacy, safety, and tolerability of PANZYGA in 40 subjects with chronic ITP and a platelet count of 20 x 10 ^9 /L or less. Subjects ranged in age from 18 to 72 years (median: 32 years); 43% were female and 57% were male. Ninety percent of the subjects were Caucasian and 10% were Asian.

Subjects received a 2 g/kg dose of PANZYGA administered as two daily 1 g/kg intravenous doses, given on 2 consecutive days. All but one patient received the maximum infusion rate of 8 mg/kg/minute, starting at 1 mg/kg/minute. Platelet counts were measured on Days 1 to 8, 15, and 22.

The study was designed to determine the response rate, defined as the percentage of subjects with an increase in platelet count to at least 50 x 10 ^9 /L within 7 days after the first infusion (responders). Additionally, maximum platelet count, the time to reach a platelet count of at least 50 x 10 ^9 /L within the first 7 days, the duration of that response (i.e., the number of days the platelet count remained in excess of 50 x 10 ^9 /L), and the regression of hemorrhages in subjects who had bleeding at baseline were observed.

Of the 36 subjects in the full analysis set, 29 (81%: 95% CI: 64%- 92%).) responded to PANZYGA with a rise in platelet count to at least 50 x 10 ^9 /L within 7 days after the first infusion. The lower bound of the overall 95% confidence interval for the response rate in all 36 subjects (64%) is above the predefined response rate of 60%.

Table 8 shows the median and mean of the maximum platelet count.

Table 8: Maximum Platelet Count (x10 ^9 /L)

 | ITP subjects (n=36)
Median and range | 196 (8 to 1067)
Mean ± standard deviation | 237 ± 205

Table 9 shows the median and mean of the time to and duration of platelet response.

Table 9: Time to and Duration of Platelet Response (Responders Only).

 | Time to Platelet Response (at least 50x10 ^9 /L) (Days) | Duration of Platelet Response (Days)
 | ITP Subjects Responders (n=29) | ITP Subjects Responders (n=29)
Median and range | 2 (1 to 4) | 14 (1 to 20)
Mean ± standard deviation | 1.8 ± 0.8 | 12.4 ± 5.8

Of the 36 subjects, 23 (64%) subjects had bleeding at baseline. Bleeding was minor in 14 subjects (39%), mild in 2 subjects (6%) and moderate in 7 subjects (19%). On Day 7, only 14% of subjects were bleeding (5/36). Persistent bleeding was mild in 1 and minor in 2 subjects. Information regarding bleeding resolution was missing in 2 subjects with moderate bleeding.

14.3 Treatment of Chronic Inflammatory Demyelinating Polyneuropathy (CIDP) in Adults

The efficacy of PANZYGA in adults with CIDP was evaluated in a prospective, double-blind, randomized, multicenter study that enrolled 142 adult subjects (between 18 and 83 years of age) with CIDP who deteriorated in the Wash-out Phase, during which the current medication (immunoglobulins or corticosteroids) was reduced gradually. Subjects were randomized 1:2:1 to receive first a loading dose of 2 g/kg, and then 0.5 g/kg, 1.0 g/kg or 2.0 g/kg PANZYGA according to their respective dose arm for 7 maintenance infusions at 3-week intervals during the 24-week Dose-evaluation Phase. Subjects in the 0.5 g/kg and 1.0 g/kg arms had the option of rescue treatment with two consecutive infusions of 2.0 g/kg Panzyga at 3-week intervals if criteria were met [ CLINICAL PHARMACOLOGY (12.3)].

Efficacy was based on the proportion of responders in the 1.0 g/kg PANZYGA arm at Week 24 relative to Baseline (Week 0). A responder was defined as a subject with a decrease of at least 1 point in the adjusted 10-point Inflammatory Neuropathy Cause and Treatment (INCAT) disability score at Week 24 relative to Baseline. The proportion of responders in the 1.0 g/kg arm was 79.71% (95% CI: 68.8, 87.5), with 55 out of 69 subjects classified as responders. Efficacy was supported by the proportion of responders in the 2.0 g/kg dose arm in the adjusted INCAT disability score, and the proportion of responders in the 1.0 g/kg and 2.0 g/kg dose arms in the grip strength, inflammatory Rasch-built Overall Disability Scale (I-RODS) and Medical Research Council (MRC) sum scores (Table 10).

Table 10: Responder rates for different efficacy scores and dose arms

 | 1.0 g/kg N=69 | 2.0 g/kg N=36
Adjusted INCAT Disability Score
Number (%) of responders | 55 (79.7%) | 33 (91.7%)
95% CI | 68.8; 87.5 | 78.2; 97.1
I-RODS
Number (%) of responders | 38 (55.1%) | 26 (72.2%)
95% CI | 43.4; 66.2 | 56; 84.2
Grip Strength
Number (%) of responders | 45 (65.2%) | 30 (83.3%)
95% CI | 53.4; 75.4 | 68.1; 92.1
MRC Sum Score
Number (%) of responders | 50 (72.5%) | 31 (86.1%)
95% CI | 61; 81.6 | 71.3; 93.9

15 REFERENCES

1. Duhem C, Dicato MA, Ries F: Side-effects of intravenous immune globulins. Clin.Exp.Immunol. 1994;97 Suppl 1:79-83.
2. Steinberger BA, Ford SM, Coleman TA: Intravenous immunoglobulin therapy results in post-infusional hyperproteinemia, increased serum viscosity, and pseudohyponatremia. Am.J Hematol. 2003;73:97-100.
3. Dalakas MC: High-dose intravenous immunoglobulin and serum viscosity: risk of precipitating thromboembolic events. Neurology 1994;44:223-226.
4. Go RS, Call TG: Deep venous thrombosis of the arm after intravenous immunoglobulin infusion: case report and literature review of intravenous immunoglobulin-related thrombotic complications. Mayo Clin Proc 2000;75:83-85.
5. Wolberg AS, Kon RH, Monroe DM, et al: Coagulation factor XI is a contaminant in intravenous immunoglobulin preparations. Am.J.Hematol. 2000;65:30-34.
6. Sekul EA, Cupler EJ, Dalakas MC: Aseptic meningitis associated with high-dose intravenous immunoglobulin therapy: frequency and risk factors. Ann Intern.Med 1994;121:259-262.
7. Kahwaji J, Barker E, Pepkowitz S, et al: Acute Hemolysis After High-Dose Intravenous Immunoglobulin Therapy in Highly HLA Sensitized Patients. Clin J Am Soc Nephrol 2009;4:1993-1997.
8. Daw Z, Padmore R, Neurath D, et al: Hemolytic transfusion reactions after administration of intravenous immune (gamma) globulin: A case series analysis. Transfusion 2008;48:1598-1601.
9. Rizk A, Gorson KC, Kenney L, et al: Transfusion-related acute lung injury after the infusion of IVIG. Transfusion 2001;41:264-268.
10. Radomski KU, Lattner G, Schmidt T, Römisch J: Pathogen Safety of a New Intravenous Immune Globulin 10% Liquid. BioDrugs 2017(2): 125-134

16 HOW SUPPLIED/STORAGE AND HANDLING

PANZYGA is supplied in 1 g, 2.5 g, 5 g, 10 g, 20 g, and 30 g single-use bottles.

The table below shows the details of available presentations of PANZYGA.

Carton NDC Number | Container NDC Number | Size | Grams Protein
0069-1011-02 | 0069-1011-01 | 10 mL | 1
0069-1109-02 | 0069-1109-01 | 25 mL | 2.5
0069-1224-02 | 0069-1224-01 | 50 mL | 5
0069-1312-02 | 0069-1312-01 | 100 mL | 10
0069-1415-02 | 0069-1415-01 | 200 mL | 20
0069-1558-02 | 0069-1558-01 | 300 mL | 30

PANZYGA is not supplied with an infusion set. If a filtered infusion set is used (not mandatory), choose a filter size of 0.2-200 microns.

Components used in the packaging of PANZYGA are not made with natural rubber latex.

Store PANZYGA for 36 months at +2°C to +8°C (36°F to 46°F) from the date of manufacture. Within its shelf-life, the product may be stored at ≤ +25°C (77°F) for up to 12 months. After storage at ≤ +25°C (77°F), either use immediately or discard the product.

Do not use after expiration date.

Do not freeze. Do not use frozen product.

PANZYGA contains no preservatives. The PANZYGA bottle is for single use only. Use promptly any bottle that has been entered or opened, and discard partially used bottles.

Dispose of any unused product or waste material in accordance with local requirements.

17 PATIENT COUNSELING INFORMATION

Inform patients of the signs and symptoms of hypersensitivity reactions including urticaria, generalized urticaria, tightness of the chest, wheezing, hypotension, and anaphylaxis, and to contact their physicians immediately if allergic symptoms occur.

Inform patients to immediately report the signs and symptoms of the following conditions to their physician:

- Decreased urine output, sudden weight gain, fluid retention/edema, and/or shortness of breath, which may suggest kidney problems (see Renal Failure (5.2)) .
- Symptoms of thrombosis which may include: pain and/or swelling of an arm or leg with warmth over the affected area, discoloration of an arm or leg, unexplained shortness of breath, chest pain or discomfort that worsens on deep breathing, unexplained rapid pulse, numbness or weakness on one side of the body (see Thrombosis (5.4))
- Severe headache, neck stiffness, drowsiness, fever, sensitivity to light, painful eye movements, nausea and vomiting (see Aseptic Meningitis Syndrome (5.5))
- Increased heart rate, fatigue, yellowing of skin or eyes and dark-colored urine (see Hemolysis (5.6))
- Trouble breathing, chest pain, blue lips or extremities, fever (see TRALI (5.7))

Inform patients that PANZYGA is made from human plasma and may contain infectious agents that can cause disease (e.g., viruses, and theoretically, the CJD agent), and that the risk of infectious agent transmission has been reduced by (a) screening plasma donors for prior exposure to viruses, (b) testing the donated plasma for viral infections and (c) inactivating and/or removing viruses during manufacture.

Inform patients that administration of PANZYGA may interfere with the response to live viral vaccines such as measles, mumps and rubella, and to notify their immunizing physician of their therapy with PANZYGA.

Manufactured by:

Octapharma Pharmazeutika Produktionsges.m.b.H.

Oberlaaer Strasse 235

1100 Vienna, Austria

Distributed by:

Pfizer Labs

Division of Pfizer Inc

New York, NY 10001

18 PACKAGE LABEL - PRINCIPAL DISPLAY PANEL

PACKAGE LABEL – PRINCIPAL DISPLAY PANEL

Immune Globulin Intravenous (Human) - ifas, 10%

Panzyga

10 mL

NDC 0069-1011-02

Carton

Panzyga

25 mL

NDC 0069-1109-02

Carton

Panzyga

50 mL

NDC 0069-1224-02

Carton

Panzyga

100 mL

NDC 0069-1312-02

Carton

Panzyga

200 mL

NDC 0069-1415-02

Carton

Panzyga

300 mL

NDC 0069-1558-02

Carton